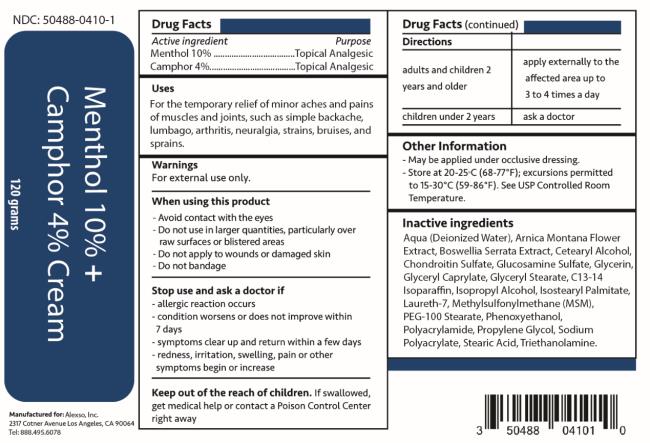 DRUG LABEL: Menthol 10 percent plus Camphor 4 percent
NDC: 50488-0410 | Form: CREAM
Manufacturer: Alexso, Inc
Category: otc | Type: HUMAN OTC DRUG LABEL
Date: 20221027

ACTIVE INGREDIENTS: MENTHOL 10 g/100 g; CAMPHOR (SYNTHETIC) 4 g/100 g
INACTIVE INGREDIENTS: WATER; ARNICA MONTANA FLOWER; INDIAN FRANKINCENSE; CETOSTEARYL ALCOHOL; CHONDROITIN SULFATE (BOVINE); GLUCOSAMINE SULFATE; GLYCERIN; GLYCERYL CAPRYLATE; GLYCERYL MONOSTEARATE; C13-14 ISOPARAFFIN; ISOPROPYL ALCOHOL; ISOSTEARYL PALMITATE; LAURETH-7; DIMETHYL SULFONE; PEG-100 STEARATE; PHENOXYETHANOL; POLYACRYLAMIDE (10000 MW); PROPYLENE GLYCOL; SODIUM POLYACRYLATE (8000 MW); STEARIC ACID; TROLAMINE

Menthol and Camphor Cream

Menthol 10% and Camphor 4% Cream
Alexso, Inc

----------

Menthol 10% and Camphor 4% Cream

Drug Facts

Purpose

Menthol 10% ……………………………………..………………….…Topical analgesic
Camphor 4% ……………………………………………………………Topical analgesic

Uses

For the temporary relief of minor aches and pains of muscles and joints, such as simple backache, lumbago, arthritis, neuralgia, strains, bruises, and sprains.

Warnings

For external use only.

When using this product

- Avoid contact with the eyes
- Do not use in large quantities, particularly over raw surfaces or blistered areas
- Do not apply to wounds or damaged skin
- Do not bandage

Stop use and ask a doctor if

- allergic reaction occurs
- condition worsens or does not improve within 7 days
- symptoms clear up and return within a few days
- redness, irritation, swelling, pain or other symptoms begin or increase

Keep out of reach of children.

If swallowed, get medical help or contact a Poison Control Center right away.

Directions

adults and children 2 years and older | apply externally to the affected area up to 3 to 4 times a day
children under 2 years | ask a doctor

Other information

- May be applied under occlusive dressing.
- Store at 20-25°C (68-77°F); excursions permitted to 15-30°C (59-86°F). See USP Controlled Room Temperature.

Inactive ingredients

Aqua (Deionized Water), Arnica Montana Flower Extract, Boswellia Serrata Extract, Cetearyl Alcohol, Chondroitin Sulfate, Glucosamine Sulfate, Glycerin, Glyceryl Caprylate, Glyceryl Stearate, C13-14 Isoparaffin, Isopropyl Alcohol, Isostearyl Palmitate, Laureth-7, Methylsulfonylmethane (MSM), PEG-100 Stearate, Phenoxyethanol, Polyacrylamide, Propylene Glycol, Sodium Polyacrylate, Stearic Acid, Triethanolamine

Menthol 10% and Camphor 4% Cream

NDC: 50488-0410-1

120 grams

Manufactured for:
Alexso, Inc
Los Angeles, CA 90064

PRINCIPAL DISPLAY PANEL

NDC 50488-0410-1
Menthol 10% +
Camphor 4% Cream
120 grams